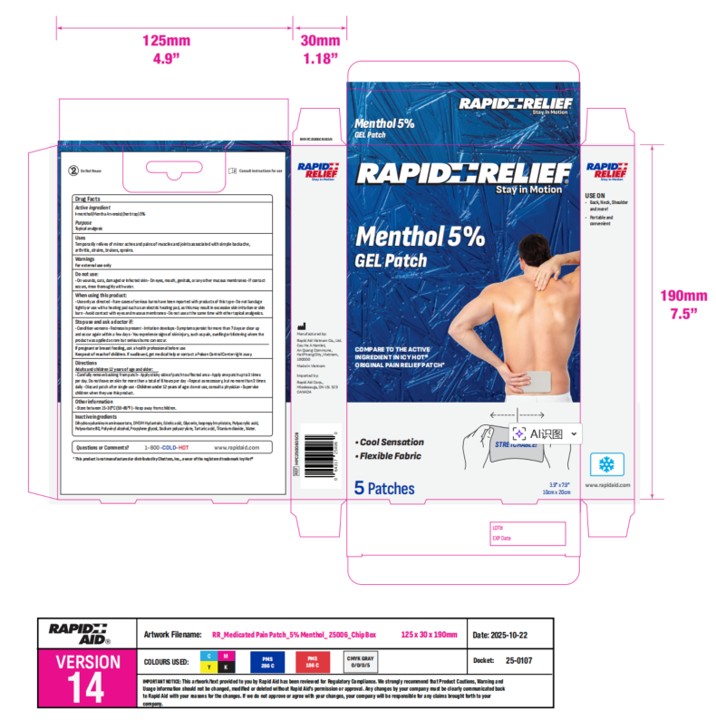 DRUG LABEL: Rapid Relief
NDC: 83569-012 | Form: PATCH
Manufacturer: RAPID AID VIET NAM COMPANY LIMITED
Category: otc | Type: HUMAN OTC DRUG LABEL
Date: 20251113

ACTIVE INGREDIENTS: MENTHOL 5 g/100 g
INACTIVE INGREDIENTS: ISOPROPYL MYRISTATE; TITANIUM DIOXIDE; POLYSORBATE 80; POLYVINYL ALCOHOL; SODIUM POLYACRYLATE (8000 MW); GLYCERIN; POLYACRYLIC ACID (800000 MW); TARTARIC ACID; EDETIC ACID; DIHYDROXYALUMINUM AMINOACETATE; POLYACRYLIC ACID (300000 MW); PROPYLENE GLYCOL; WATER; DMDM HYDANTOIN

Active Ingredient(s)

Menthol 5% w/w.

Purpose

Topical analgesic

Use

Temporary relives of minor aches and pains of muscles and joints associated with simple backache, arthritis, strains, bruises, sprains.

Warnings

For external use only.

Do not use

On wounds, cuts, damaged or infected skin
On eyes, mouth, genitals, or any other mucous membranes

If contact occurs, rinse thoroughly with water.

When using this product:

Use only as directed

Rear cases of serious burns have been reported with products of this type

Do not bandage tightly or use with a heating pad such as an electric heating pad, as this may result in excessive skin irritation or skin burn

Avoid contact with eyes and mucous membranes

Do not apply to wounds or damaged skin.

Do not use at the same time as other topical analgesics.

Stop use and ask a doctor if:

Condition worsens

Redness is present

Irritation develops

Symptoms persist for more than 7 days or clear up and occur again within a few days

You experience signs of skin injury, such as pain, swelling or blistering where the product was applied as rare but the serious burns can occur.

If pregnant or breastfeeding, ask a health professional before use.

Directions

Adults and children 12 years of age and older:

Carefully remove backing from patch

Apply sticky side of patch to affected area.

Do not leave on skin for more than a total of 8 hours per day.

Repeat as necessary, but no more than 3 times daily .

Discard patch after single use.

Children under 12 years of age: do not use, consult a physician.

Supervise children when they use this product.

STORAGE AND HANDLING

Store between 15-30℃(59-86℉) keep away from children

Inactive ingredients

Dihydroxyaluminum aminoacetate, DMDM hydantoin, Edetic acid, Glycerin, Isopropyl myristate, Polyacrylic acid, Polysorbate 80, Polyvinyl alcohol, Propylene glycol, Sodium polyacrylate, Tartaric acid, Titanium dioxide, Water

KEEP OUT OF REACH OF CHILDREN

If swallowed, get medical help or contact a Poison Control Center right away.